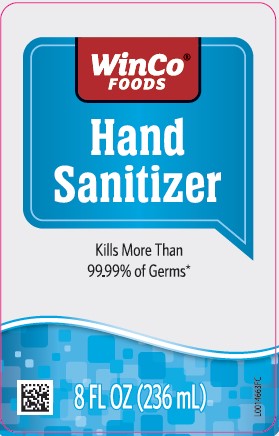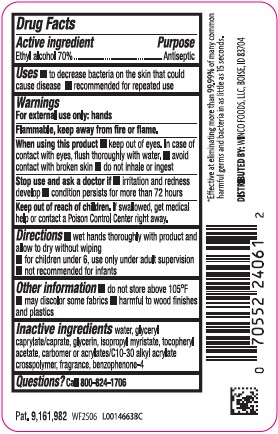 DRUG LABEL: Hand Sanitizer
NDC: 67091-107 | Form: GEL
Manufacturer: WinCo Foods, LLC
Category: otc | Type: HUMAN OTC DRUG LABEL
Date: 20260212

ACTIVE INGREDIENTS: ALCOHOL 70 mL/100 mL
INACTIVE INGREDIENTS: WATER; GLYCERYL CAPRYLATE/CAPRATE; GLYCERIN; ISOPROPYL MYRISTATE; .ALPHA.-TOCOPHEROL ACETATE; CARBOMER COPOLYMER TYPE B (ALLYL PENTAERYTHRITOL CROSSLINKED); SULISOBENZONE

WinCo 370.001/370AB - AE rev 1
Advanced Hand Sanitizer

Active Ingredient

Ethyl alcohol 70%

Purpose

Antiseptic

Uses

- to decrease bacteria on the skin that could cause disease
- recommended for repeated use

Warnings

For external use only: hands

Flammable. Keep away from heat and flame.

When using this product

- keep out of eyes. In case of contact with eyes, flush thoroughly with water.
- avoid contact with broken skin
- do not inhale or ingest

Stop use and ask a doctor if

- irritation and redness develop
- condition persists for more than 72 hours

Keep out of reach of children.

If swallowed, get medical help or contact a Poison Control Center right away.

Directions

- wet hands thoroghly with product and allow to dry without wiping
- for children under 6, use only under adult supervision
- not recommended for infants

Other information

- do not store above 105⁰ F
- may discolor some fabrics
- harmful to wood finishes and plastics

Inactive ingredients

water, glyceryl caprylate/caprate, glycerin, isopropyl myristate, tocopheryl acetate, carbomer or acrylates/C10-30 alkyl acrylate crosspolymer, fragrance, benzophenone-4

Questions?

Call 800-824-1706

ADVERSE REACTION

*Effective at eliminating more than 99.99% of many common harmful germs and bacteria in as little as 15 seconds.

DISTRIBUTED BY: WINCO FOODS, LLC, BOISE, ID 83704

Pat. 9,161,982

principal display panel

WinCo®FOODS

HANDS SANITIZER

Kills More Than 99.99% of Germs*

8 FL OZ (236 mL)